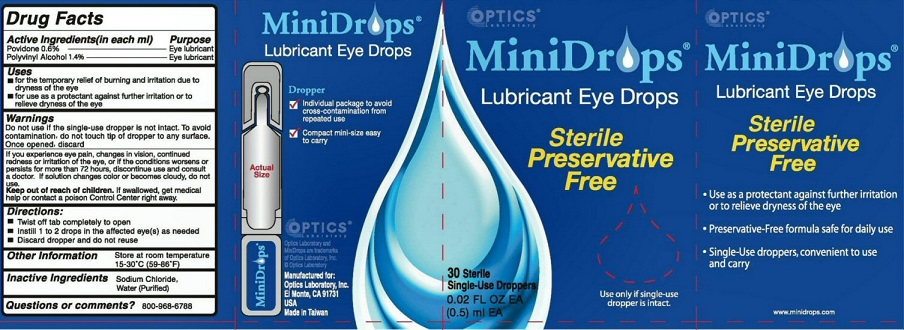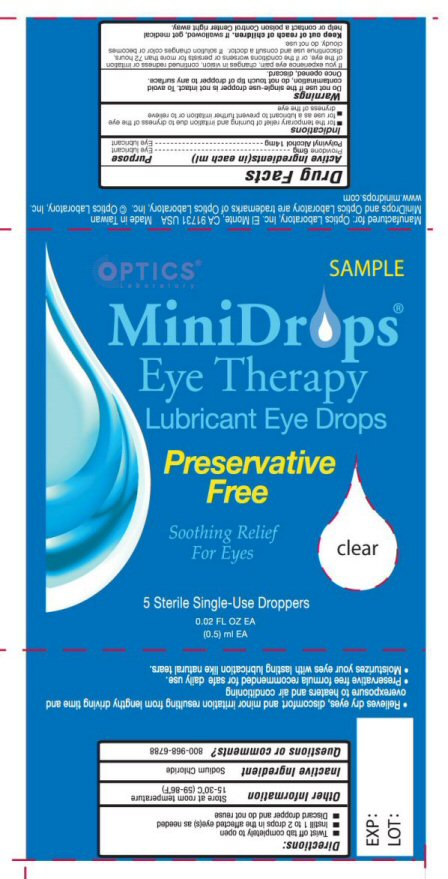 DRUG LABEL: MINIDROPS
NDC: 64108-212 | Form: LIQUID
Manufacturer: Optics Laboratory, Inc
Category: otc | Type: HUMAN OTC DRUG LABEL
Date: 20260203

ACTIVE INGREDIENTS: POVIDONE, UNSPECIFIED 6 mg/1 mL; POLYVINYL ALCOHOL 14 mg/1 mL
INACTIVE INGREDIENTS: SODIUM CHLORIDE 0.9 mg/1 mL; WATER 97.1 mg/1 mL

ACTIVE INGREDIENTS SECTION

POVIDONE 0.6%

POLYVINYL ALCOHOL 1.4%

PURPOSE SECTION

EYE LUBRICANT

KEEP OUT OF REACH OF CHILDREN SECTION

KEEP OUT OF REACH OF CHILDREN. IF SWALLOWED, GET MEDICAL HELP OR CONTACT A POISON CONTROL CENTER RIGHT AWAY.

INDICATIONS AND USE SECTION

USES FOR TEMPORARY RELIEF OF BURNING AND IRRITATION DUE TO DRYNESS OF THE EYE

FOR USE AS A PROTECTANT AGAINST FURTHER IRRITATION OR TO RELIEVE DRYNESS OF THE EYE

WARNINGS SECTION

WARNINGS DO NOT USE IF THE SINGLE-DOSE DROPPER IS NOT INTACT. TO AVOID CONTAMINATION, DO NOT TOUCH TIP OF DROPPER TO ANY SURFACE. ONCE OPENED, DISCARD.

IF YOU EXPERIENCE EYE PAIN, CHANGES IN VISION, CONTINUED REDNESS OR IRRITATION OF THE EYE, OR IF THE CONDITIONS WORSENS OR PERSISTS FOR MORE THAN 72 HOURS, DISCONTINUE USE AND CONSULT A DOCTOR. IF SOLUTION CHANGES COLOR OR BECOMES CLOUDY, DO NOT USE

OTHER INFORMATION STORE AT ROOM TEMPERATURE 15-30 DEGREES C (59-86 DEGREES F)

DOSAGE AND ADMINISTRATION SECTION

DIRECTIONS TWIST OFF TAB COMPLETELY TO OPEN. INSTILL 1 TO 2 DROPS IN THE AFFECTED EYE(S) AS NEEDED. DISCARD DROPPER AND DO NOT REUSE.

INACTIVE INGREDIENTS SECTION

SODIUM CHLORIDE, WATER (PURIFIED)

QUESTIONS SECTION

QUESTIONS OR COMMENTS? 800-968-6788

PACKAGE LABEL

MINIDROPS LUBRICANT EYE DROPS DROPPER

INDIVIDUAL PACKAGE TO AVOID CROSS-CONTAMINATION FROM REPEATED USE

COMPACT MINI-SIZE EASY TO CARRY OPTICS MANUFACTURED FOR OPTICS LABORATORY INC.EL MONTE, CA 91731 USA MADE IN TAIWAN

STERILE PRESERVATIVE FREE USE ONLY IF SINGLE-USE DROPPER IS INTACT USE AS A PROTECTANT AGAINST FURTHER IRRITATION OR TO RELIEVE DRYNESS OF THE EYE PRESERVATIVE-FREE FORMULA SAFE FOR DAILY USE SINGLE-USE DROPPERS, CONVENIENT TO USE AND CARRY

MINIDROPS AND OPTIC LABORATORY ARE TRADEMARKS OF OPTIC LABORATORY INC

res